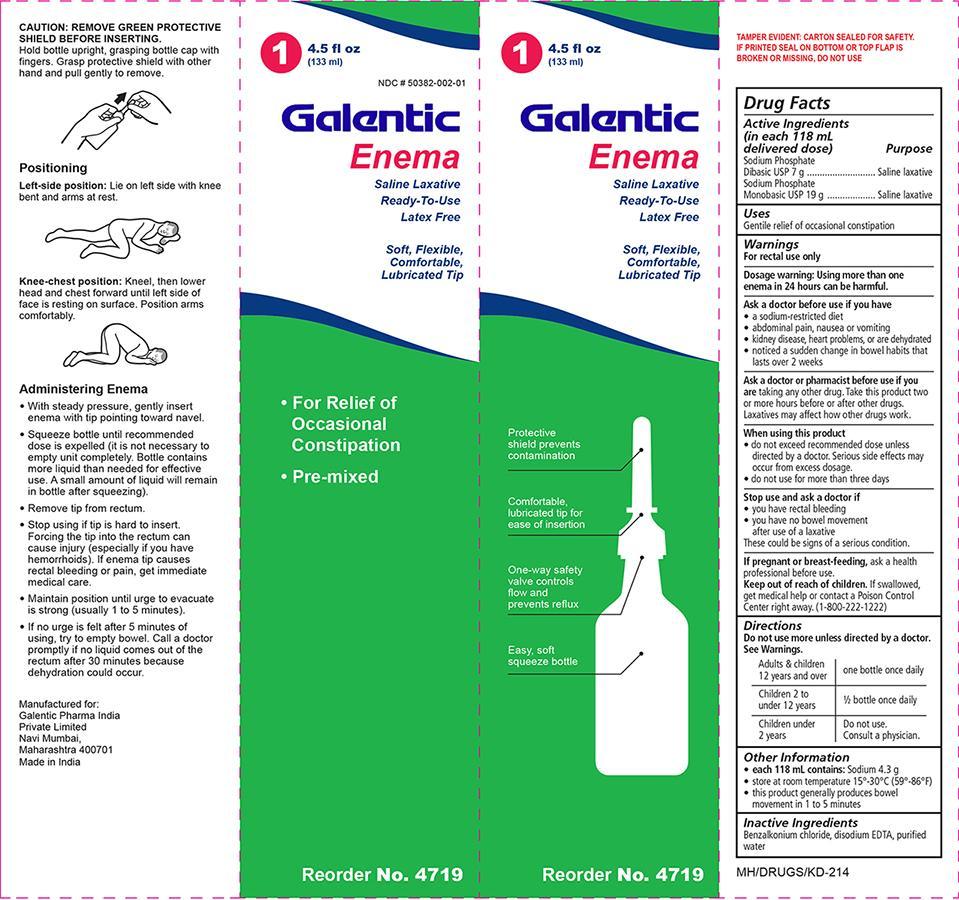 DRUG LABEL: Saline Enema
NDC: 50382-002 | Form: ENEMA
Manufacturer: Galentic Pharma (India) Priva Te Ltd.
Category: otc | Type: HUMAN OTC DRUG LABEL
Date: 20130808

ACTIVE INGREDIENTS: SODIUM PHOSPHATE, DIBASIC 7 g/118 mL; SODIUM PHOSPHATE, MONOBASIC 19 g/118 mL
INACTIVE INGREDIENTS: WATER

Enema, Saline

Active Ingredient

(in each 118 mL delivered dose)

Dibasic sodium phosphate 7g

Monobasic sodium phosphate 19g

Purpose

Saline laxative

Uses:

- Gentle relief of occasional constipation

Warnings:

For rectal use only

Dosage Warning: Using more than one enema in 24 hours can be harmful.

As a doctor before use if you have:

- a sodium-restricted diet
- abdominal pain, nausea or vomiting
- kidney disease, heart problems, or are dehydrated
- notice a sudden change in bowel habits that persists over a period of 2 weeks

- If pregnant or breast feeding, ask a health professional before use.

Ask a doctor or pharmacist before use if you are

- taking any other drug
- take this product two or more hours before or after other drugs

Laxatives may affect how other drugs work.

Stop use and ask a doctor if:

- If you have rectal bleeding
- you have no bowel movement after use of a laxative. This may indicate a serious condition

Keep out of reach of children

If swallowed, get medical help or contact a Poison Control Center right away. (1-800-222-1222)

Other information:

- Each 118 mL contains: Sodium 4.3 g
- Store at room temperature 15 Deg C - 30 Deg C (59 Deg F - 86 Deg F)
- This product generally produces bowel movement in 15 minutes.

Directions

Do not use more unless directed by a doctor

See Warnings

Adults and children 12 years and older - 1 bottle

Children 2 to under 12 years - 1/2 bottle

Children under 2 years - Do not use. Consult a physician.

Inactive ingredient

Water

Indications and Usage

- For relief of occasional constipation

When using this product

- Do not exceed recommended dose unless directed by a doctor. Serious side effects may occur from excess dosage.
- Do not use more than three days.

Use of this product:

CAUTION: REMOVE GREEN PROTECTIVE SHIELD BEFORE INSERTING

Hold bottle upright, grasping bottle cap with fingers. Grasp protective shield with other hand and pull gently to remove.

Positioning

Left-side position: Lie on left side with knees bent and arms at rest. (see diagram on box)

Knee-chest position: Kneel, then lower headand chest forward until left side of face is resting on surface. Position arms comfortably. (see diagram on box)

Administering Enema

- With steady pressure, gently insert enema with tip pointing toward navel.
- Squeeze bottle until recommended dose is expelled (it is not necessary to empty unit completely. Bottle contains more liquid than needed for effective use. A small amount of liquid will remain in bottle after squeezing).
- Remove tip from rectum.
- Stop using if tip is hard to insert. Forcing the tip into the rectum can cause injury (especially if you have hemorrhoids). If enema tip causes rectal bleeding or pain, get immediate medical care.
- Maintain position until urge to evacuate is strong (usually 1 to 5 minutes).
- If no urge is felt after 5 minutes of using, try to empty bowel. Call a doctor promptly if no liquid comes out of the rectum after 30 minutes because dehydration could occur.

Principal Display Panel

Gal Saline Enema.jpg

Saline enema